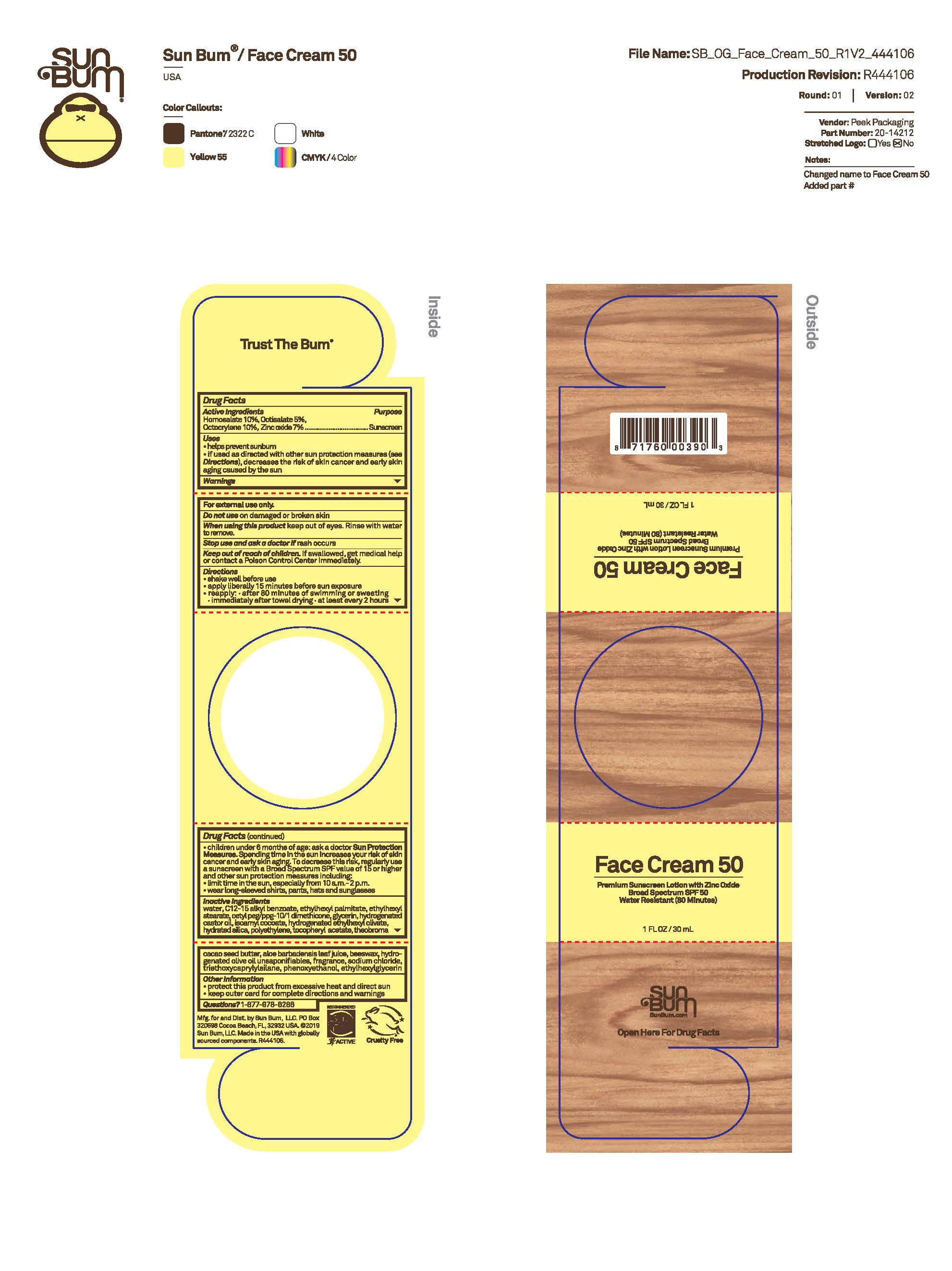 DRUG LABEL: Sun Bum Face Cream 50 Premium Sunscreen
NDC: 69039-799 | Form: CREAM
Manufacturer: Sun Bum, LLC
Category: otc | Type: HUMAN OTC DRUG LABEL
Date: 20250814

ACTIVE INGREDIENTS: OCTOCRYLENE 100 mg/1 mL; ZINC OXIDE 70 mg/1 mL; HOMOSALATE 100 mg/1 mL; OCTISALATE 50 mg/1 mL
INACTIVE INGREDIENTS: HYDROGENATED CASTOR OIL; TRIETHOXYCAPRYLYLSILANE; ALOE BARBADENSIS LEAF; ISOAMYL COCOATE; SODIUM CHLORIDE; POLYETHYLENE; THEOBROMA CACAO (COCOA) SEED BUTTER; HYDRATED SILICA; HYDROGENATED ETHYLHEXYL OLIVATE; BEESWAX; GLYCERIN; .ALPHA.-TOCOPHEROL ACETATE; HYDROGENATED OLIVE OIL UNSAPONIFIABLES; PHENOXYETHANOL; WATER; CETYL PEG/PPG-10/1 DIMETHICONE (HLB 2); ETHYLHEXYLGLYCERIN; ETHYLHEXYL STEARATE; C12-15 ALKYL BENZOATE; ETHYLHEXYL PALMITATE

Sun Bum Face Cream 50 Premium Sunscreen

Active Ingredients

Homosalate 10%, Octisalate 5%, Octocrylene 10%, Zinc Oxide 7%

Purpose

Sunscreen

Uses

• helps prevent sunburn • if used as directed with other sun protection measures, (see Directions) decreases the risk of skin cancer and early skin aging caused by the sun

Warnings

For external use only

Do not use on damaged or broken skin

When using this product keep out of eyes. Rinse with water to remove.

Stop use and ask a doctor if rash occurs

Keep out of reach of children. If swallowed, get medical help or contact a Poison Control Center immediately.

Warnings

Keep Out Of Reach Of Children

Directions

• shake well before use

• apply liberally 15 minutes before sun exposure

• reapply: • after 80 minutes of swimming or sweating • immediately after towel drying • at least every 2 hours

• children under 6 months of age: ask a doctor

• Sun Protection Measures. Spending time in the sun increases your risk of skin cancer and early skin aging. To decrease this risk, regularly use a sunscreen with a Broad Spectrum SPF value of 15 or higher and other sun protection measures including:

• limit time in the sun, especially from 10 a.m.- 2 p.m.

• wear long-sleeved shirts, pants, hats and sunglasses

Directions

• shake well before use

• apply liberally 15 minutes before sun exposure

Other Information

protect this product from excessive heat and direct sun

Inactive Ingredients

Water, C12-15 Alkyl Benzoate, Ethylhexyl Palmitate, Ethylhexyl Stearate, Cetyl PEG/PPG-10/1 Dimethicone, Glycerin, Hydrogenated Castor Oil, Isoamyl Cocoate, Hydrogenated Ethylhexyl Olivate, Hydrated Silica, Polyethylene, Tocopheryl Acetate, Theobroma Cacao Seed Butter, Aloe Barbadensis Leaf Juice, Beeswax, Hydrogenated Olive Oil Unsaponifiables, Fragrance, Sodium Chloride, Triethoxycaprylylsilane, Phenoxyethanol, Ethylhexylglycerin

Questions?

1-877-978-6286